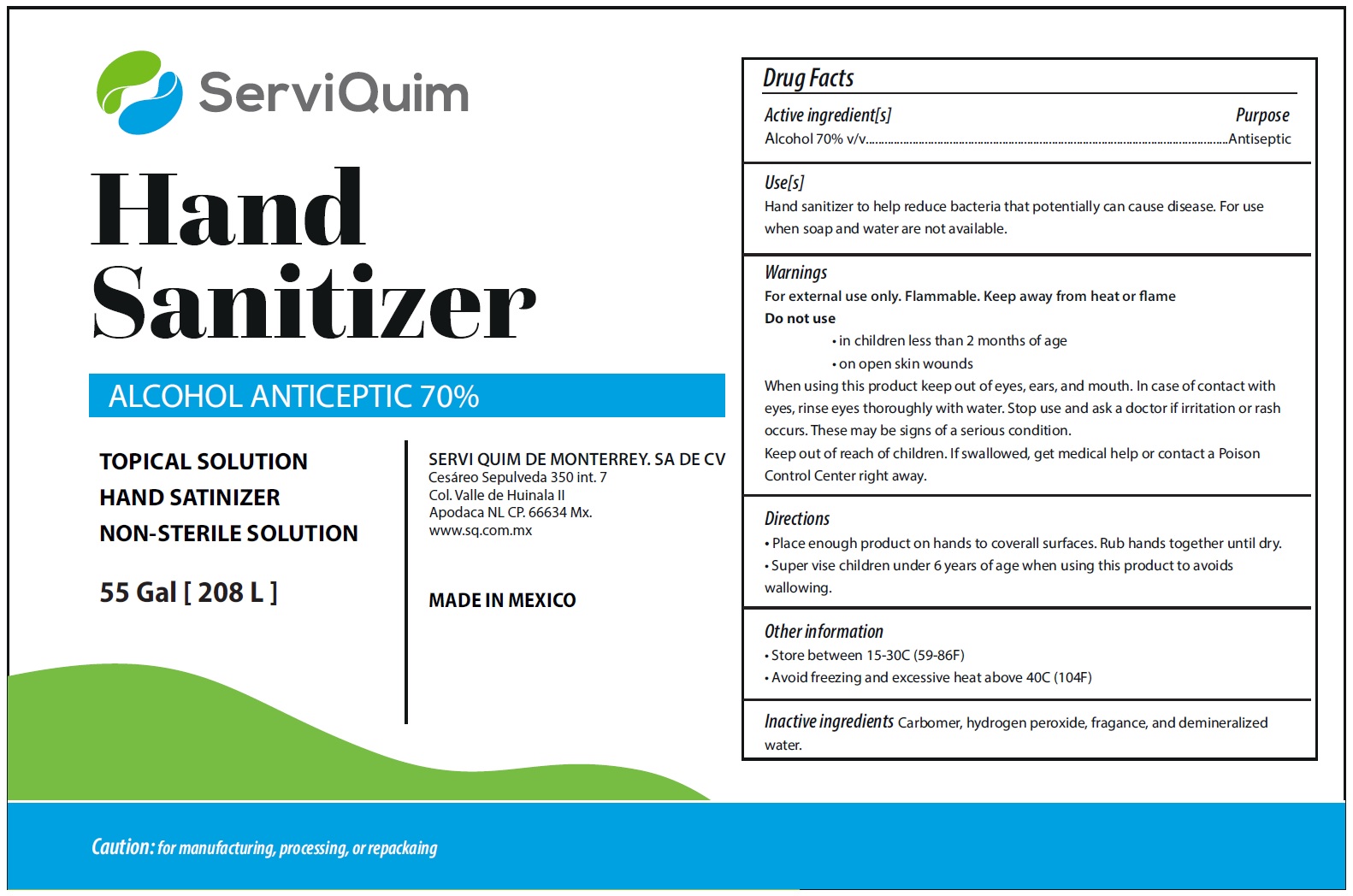 DRUG LABEL: Hand Sanitizer 70 Alcohol
NDC: 79324-000 | Form: GEL
Manufacturer: Servi Quim de Monterrey, S.A. de C.V.
Category: otc | Type: HUMAN OTC DRUG LABEL
Date: 20231028

ACTIVE INGREDIENTS: ALCOHOL 0.7 mL/1 mL
INACTIVE INGREDIENTS: CARBOMER HOMOPOLYMER, UNSPECIFIED TYPE; HYDROGEN PEROXIDE; WATER

Hand Sanitizer 70% Alcohol

Active ingredient[s]

Alcohol 70% v/v

Purpose

Antiseptic

Use[s]

Hand sanitizer to help reduce bacteria that potentially can cause disease. For use when soap and water not available.

Warnings

For external use only. Flammable. Keep away from heat or flame

Do not use

- in children less than 2 months of age
- on open skin wounds

When using this product

keep out of eyes, ears, and mouth. In case of contact with eyes, rinse eyes thoroughly with water.

Stop use and ask a doctor

if irritation or rash occurs. These may be signs or a serious condition.

Keep out of reach of children.

If swallowed, get medical help or contact a Poison Control Center right away.

Directions

- Place enough product on hands to coverall surfaces. Rub hands together until dry.
- Super vise children under 6 years of age when using this product to avoids wallowing.

Other information

- Store between 15-30C (59-86F)
- Avoid freezing and excessive heat above 40C (104F)

Inactive ingredients

Carbomer,hydrogen peroxide,fragance,and demineralized water.